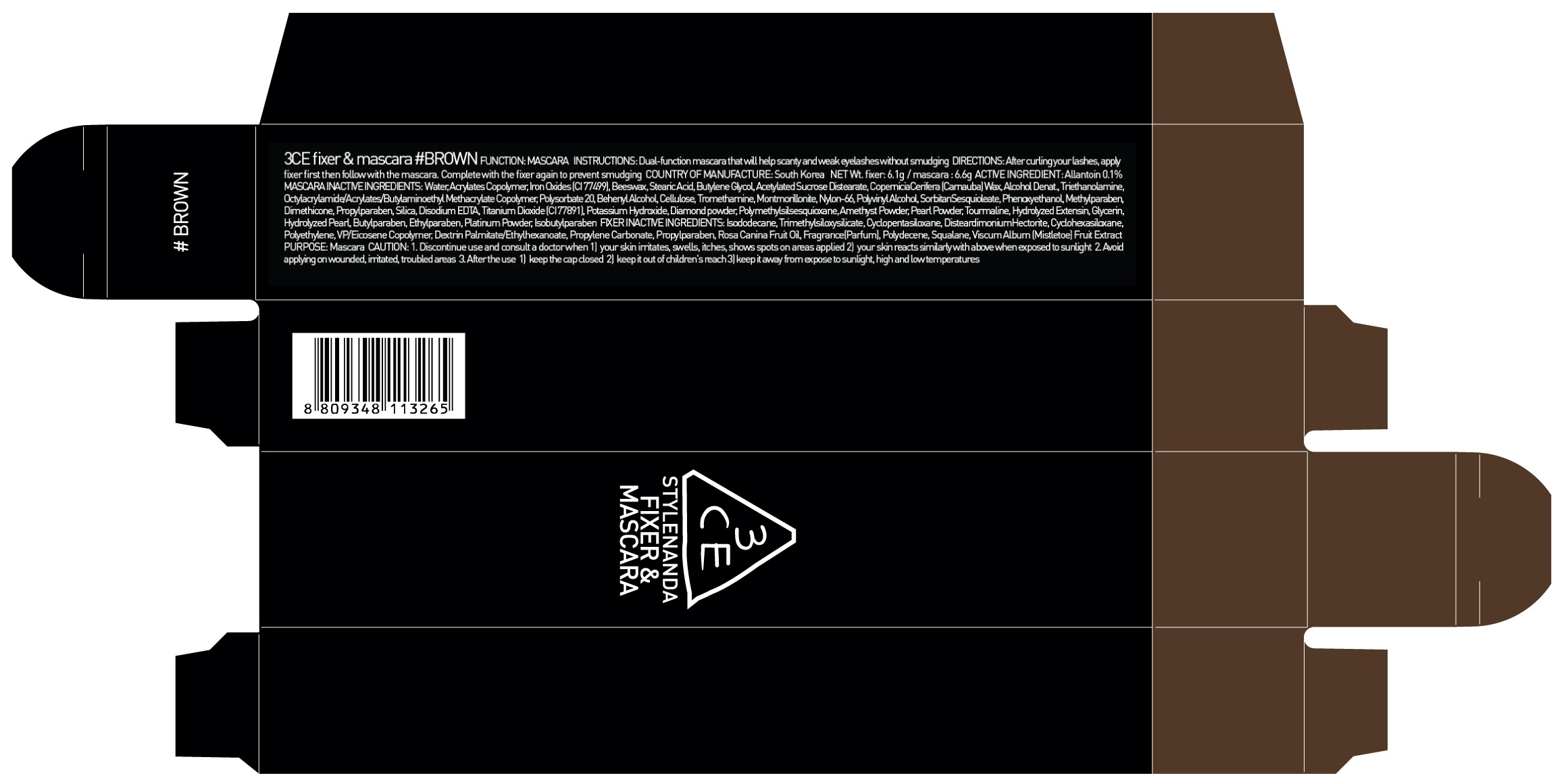 DRUG LABEL: 3CE FIXER AND MASCARA BROWN
NDC: 60764-134 | Form: LIQUID
Manufacturer: Nanda Co., Ltd
Category: otc | Type: HUMAN OTC DRUG LABEL
Date: 20161017

ACTIVE INGREDIENTS: Allantoin 0.006 g/6.6 g
INACTIVE INGREDIENTS: Water; Isododecane

ACTIVE INGREDIENT

Active Ingredient: Allantoin 0.1%

INACTIVE INGREDIENT

Mascara Inactive Ingredients: Water, Acrylates Copolymer, Beeswax, Stearic Acid, Iron Oxides (CI 77499), Butylene Glycol, Acetylated Sucrose Distearate, CoperniciaCerifera (Carnauba) Wax, Alcohol Denat., Triethanolamine, Octylacrylamide/Acrylates/Butylaminoethyl Methacrylate Copolymer, Iron Oxides (CI 77491), Titanium Dioxide (CI 77891), Polysorbate 20, Behenyl Alcohol, Cellulose, Iron Oxides (CI 77492), Tromethamine, Montmorillonite, Nylon-66, Polyvinyl Alcohol, SorbitanSesquioleate, Phenoxyethanol, Methylparaben, Dimethicone, Propylparaben, Silica, Disodium EDTA, Potassium Hydroxide, Diamond powder, Polymethylsilsesquioxane, Amethyst Powder, Pearl Powder, Tourmaline, Hydrolyzed Extensin, Glycerin, Hydrolyzed Pearl, Butylparaben, Ethylparaben, Platinum Powder, Isobutylparaben

Fixer Inactive Ingredients: Isododecane, Trimethylsiloxysilicate, Cyclopentasiloxane, DisteardimoniumHectorite, Cyclohexasiloxane, Polyethylene, VP/Eicosene Copolymer, Dextrin Palmitate/Ethylhexanoate, Propylene Carbonate, Propylparaben, Rosa Canina Fruit Oil, Fragrance(Parfum), Polydecene, Squalane, Viscum Album (Mistletoe) Fruit Extract

PURPOSE

Purpose: Mascara

CAUTION

CAUTION: 1. Discontinue use and consult a doctor when - your skin irritates, swells, itches, shows spots on areas applied - your skin reacts similarly with above when exposed to sunlight 2. Avoid applying on wounded, irritated, troubled areas 3. After the use - keep the cap closed - keep it out of children's reach - keep it away from expose to sunlight, high and low temperatures

KEEP OUT OF REACH OF CHILDREN

keep it out of children's reach

INSTRUCTIONS

INSTRUCTIONS: Dual-function mascara that will help scanty and weak eyelashes without smudging.

Directions

Directions: After curling your lashes, apply fixer first then follow with the mascara. Complete with the fixer again to prevent smudging.